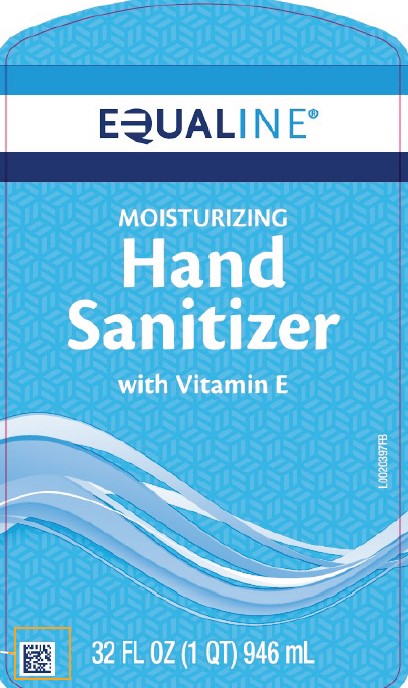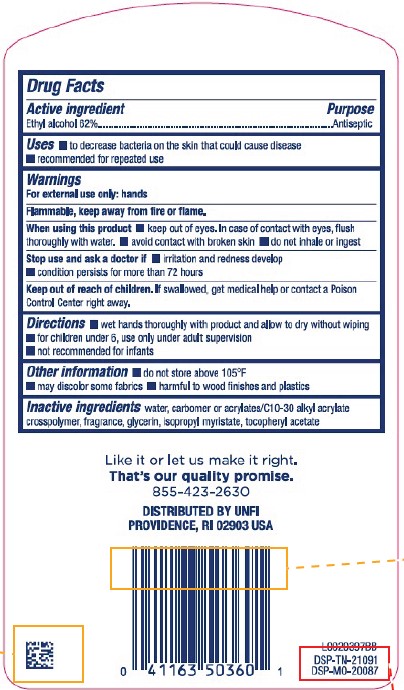 DRUG LABEL: Alcohol
NDC: 41163-975 | Form: LIQUID
Manufacturer: United Natural Foods, Inc. dba UNFI
Category: otc | Type: HUMAN OTC DRUG LABEL
Date: 20260217

ACTIVE INGREDIENTS: ALCOHOL 62 mL/100 mL
INACTIVE INGREDIENTS: WATER; CARBOMER INTERPOLYMER TYPE A (ALLYL SUCROSE CROSSLINKED); GLYCERIN; ISOPROPYL MYRISTATE; TOCOPHEROL

Equaline 849.001/849AA-AG Rev1, BA
Moisturizing Hand Sanitizer

Active ingredient

Ethyl Alcohol 62%

Purpose

Antiseptic

Uses

- to decrease bacteria on the skin that could cause disease
- recommended for repeated use

Warnings

For external use only: hands

Flammable, keep away from fire or flame.

When using this product

- keep out of eyes. In case of contact with eyes, flush thoroughly with water.
- avoid contact with broken skin
- do not inhale or ingest

Stop use and ask a doctor if

- irritation and redness develop
- condition persists for more than 72 hours

Keep out of reach of children.

If swallowed, get medical help or contact a Poison Control Center right away.

Directions

- wet hands thoroughly with product and allow to dry without wiping
- for children under 6, use only under adult supervision
- not recommended for infants

Other information

- do not store above 105⁰F
- may discolor some fabrics
- harmful to wood finishes and plastics

Inactive ingredients

water, carbomer and/or acrylates/C10-30 alkyl acrylate crosspolymer, fragrance, glycerin, isopropyl myristate, tocopheryl acetate

ADVERSE REACTION

Like it or let us make it right.

That's our quality promise.

855-423-2630

DISTRIBUTED BY UNFI

PROVIDENCE, RI 02908 USA

DSP-TN-21091

DSP-MO-20087

Principal display panel

EQUALINE®

MOISTURIZING

Hand Sanitizer

with Vitamin E

32 FL OZ (1 QT) 946 mL